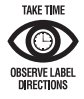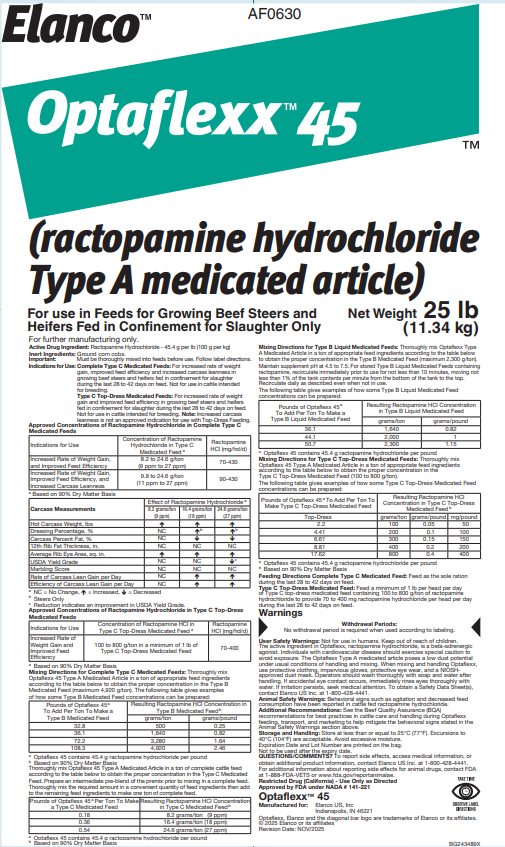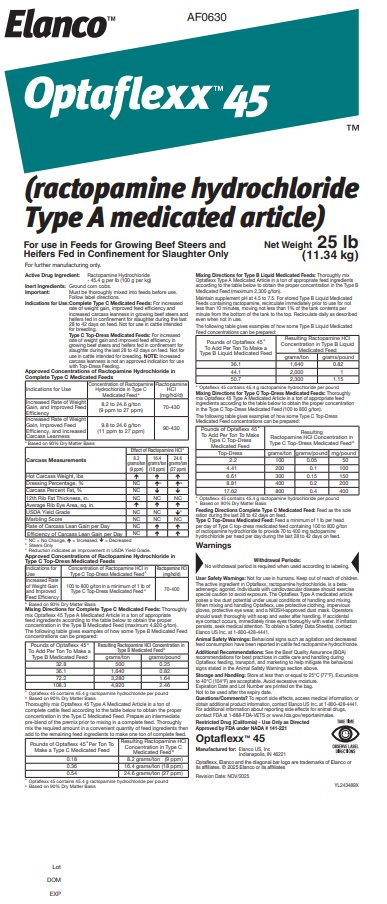 DRUG LABEL: Optaflexx 45
NDC: 58198-0630 | Form: POWDER
Manufacturer: Elanco US Inc.
Category: animal | Type: OTC TYPE A MEDICATED ARTICLE ANIMAL DRUG LABEL
Date: 20260116

ACTIVE INGREDIENTS: ractopamine hydrochloride 45.4 g/0.45 kg

Elanco™

AF0630

Optaflexx™45

(ractopamine hydrochloride Type A medicated article)

For use in Feeds for Growing Beef Steers and Heifers Fed in Confinement for Slaughter Only

Net Weight 25 lb
(11.34 kg)

For further manufacturing only.

Active Drug Ingredient: Ractopamine Hydrochloride - 45.4 g per lb (100 g per kg)

Inert Ingredients: Ground corn cobs.

Important: Must be thoroughly mixed into feeds before use. Follow label directions.

INDICATIONS AND USAGE

Indications for Use: Complete Type C Medicated Feeds: For increased rate of weight gain, improved feed efficiency and increased carcass leanness in growing beef steers and heifers fed in confinement for slaughter during the last 28 to 42 days on feed. Not for use in cattle intended for breeding.

Type C Top-Dress Medicated Feeds: For increased rate of weight gain and improved feed efficiency in growing beef steers and heifers fed in confinement for slaughter during the last 28 to 42 days on feed. Not for use in cattle intended for breeding. Note: Increased carcass leanness is not an approved indication for use with Top-Dress Feeding.

Approved Concentrations of Ractopamine Hydrochloride in Complete Type C Medicated Feeds

Indications for Use | Concentration of Ractopamine Hydrochloride in Type C Medicated Feed a | Ractopamine HCl (mg/hd/d)
Increased Rate of Weight Gain, and Improved Feed Efficiency | 8.2 to 24.6 g/ton (9 ppm to 27 ppm) | 70-430
Increased Rate of Weight Gain, Improved Feed Efficiency, and Increased Carcass Leanness | 9.8 to 24.6 g/ton (11 ppm to 27 ppm) | 90-430
a Based on 90% Dry Matter Basis

Carcass Measurements | Effect of Ractopamine Hydrochloride a
Carcass Measurements | 8.2 grams/ton (9 ppm) | 16.4 grams/ton (18 ppm) | 24.6 grams/ton (27 ppm)
Hot Carcass Weight, lbs | ↑ | ↑ | ↑
Dressing Percentage, % | NC | ↑b | ↑b
Carcass Percent Fat, % | NC | ↓ | ↓
12th Rib Fat Thickness, in. | NC | NC | NC
Average Rib Eye Area, sq. in. | ↑ | ↑ | ↑
USDA Yield Grade | NC | NC | ↓c
Marbling Score | NC | NC | NC
Rate of Carcass Lean Gain per Day | NC | ↑ | ↑
Efficiency of Carcass Lean Gain per Day | NC | ↑ | ↑
a NC = No Change, ↑ = Increased, ↓ = Decreased
b Steers Only
c Reduction indicates an improvement in USDA Yield Grade.

Approved Concentrations of Ractopamine Hydrochloride in Type C Top-Dress Medicated Feeds

Indications for Use | Concentration of Ractopamine HCl in Type C Top-Dress Medicated Feed a | Ractopamine HCl (mg/hd/d)
Increased Rate of Weight Gain and Improved Feed Efficiency | 100 to 800 g/ton in a minimum of 1 lb of Type C Top-Dress Medicated Feed | 70-400
a Based on 90% Dry Matter Basis

Mixing Directions for Complete Type C Medicated Feeds: Thoroughly mix Optaflexx 45 Type A Medicated Article in a ton of appropriate feed ingredients according to the table below to obtain the proper concentration in the Type B Medicated Feed (maximum 4,920 g/ton). The following table gives examples of how some Type B Medicated Feed concentrations can be prepared:

Pounds of Optaflexx 45 a To Add Per Ton To Make a Type B Medicated Feed | Resulting Ractopamine HCl Concentration in Type B Medicated Feed b
Pounds of Optaflexx 45 a To Add Per Ton To Make a Type B Medicated Feed | grams/ton | grams/pound
32.8 | 500 | 0.25
36.1 | 1,640 | 0.82
72.2 | 3,280 | 1.64
108.3 | 4,920 | 2.46
a Optaflexx 45 contains 45.4 g ractopamine hydrochloride per pound
b Based on 90% Dry Matter Basis

Thoroughly mix Optaflexx 45 Type A Medicated Article in a ton of complete cattle feed according to the table below to obtain the proper concentration in the Type C Medicated Feed. Prepare an intermediate pre-blend of the premix prior to mixing in a complete feed. Thoroughly mix the required amount in a convenient quantity of feed ingredients then add to the remaining feed ingredients to make one ton of complete feed.

Pounds of Optaflexx 45 a Per Ton To Make a Type C Medicated Feed | Resulting Ractopamine HCl Concentration in Type C Medicated Feed b
0.18 | 8.2 grams/ton (9 ppm)
0.36 | 16.4 grams/ton (18 ppm)
0.54 | 24.6 grams/ton (27 ppm)
a Optaflexx 45 contains 45.4 g ractopamine hydrochloride per pound
b Based on 90% Dry Matter Basis

Mixing Directions for Type B Liquid Medicated Feeds: Thoroughly mix Optaflexx Type A Medicated Article in a ton of appropriate feed ingredients according to the table below to obtain the proper concentration in the Type B Medicated Feed (maximum 2,300 g/ton).

Maintain supplement pH at 4.5 to 7.5. For stored Type B Liquid Medicated Feeds containing ractopamine, recirculate immediately prior to use for not less than 10 minutes, moving not less than 1% of the tank contents per minute from the bottom of the tank to the top. Recirculate daily as described even when not in use.

The following table gives examples of how some Type B Liquid Medicated Feed concentrations can be prepared:

Pounds of Optaflexx 45 a To Add Per Ton To Make a Type B Liquid Medicated Feed | Resulting Ractopamine HCl Concentration in Type B Liquid Medicated Feed
Pounds of Optaflexx 45 a To Add Per Ton To Make a Type B Liquid Medicated Feed | grams/ton | grams/pound
36.1 | 1,640 | 0.82
44.1 | 2,000 | 1
50.7 | 2,300 | 1.15
a Optaflexx 45 contains 45.4 g ractopamine hydrochloride per pound

Mixing Directions for Type C Top-Dress Medicated Feeds: Thoroughly mix Optaflexx 45 Type A Medicated Article in a ton of appropriate feed ingredients according to the table below to obtain the proper concentration in the Type C Top-Dress Medicated Feed (100 to 800 g/ton).

The following table gives examples of how some Type C Top-Dress Medicated Feed concentrations can be prepared:

Pounds of Optaflexx 45 a To Add Per Ton To Make Type C Top-Dress Medicated Feed | Resulting Ractopamine HCl Concentration in Type C Top-Dress Medicated Feed b
Top-Dress | grams/ton | grams/pound | mg/pound
2.2 | 100 | 0.05 | 50
4.41 | 200 | 0.1 | 100
6.61 | 300 | 0.15 | 150
8.81 | 400 | 0.2 | 200
17.62 | 800 | 0.4 | 400
a Optaflexx 45 contains 45.4 g ractopamine hydrochloride per pound
b Based on 90% Dry Matter Basis

Feeding Directions Complete Type C Medicated Feed: Feed as the sole ration during the last 28 to 42 days on feed.

Type C Top-Dress Medicated Feed: Feed a minimum of 1 lb per head per day of Type C top-dress medicated feed containing 100 to 800 g/ton of ractopamine hydrochloride to provide 70 to 400 mg ractopamine hydrochloride per head per day during the last 28 to 42 days on feed.

Warnings

Withdrawal Periods:

No withdrawal period is required when used according to labeling.

User Safety Warnings: Not for use in humans. Keep out of reach of children. The active ingredient in Optaflexx, ractopamine hydrochloride, is a beta-adrenergic agonist. Individuals with cardiovascular disease should exercise special caution to avoid exposure. The Optaflexx Type A medicated article poses a low dust potential under usual conditions of handling and mixing. When mixing and handling Optaflexx, use protective clothing, impervious gloves, protective eye wear, and a NIOSH-approved dust mask. Operators should wash thoroughly with soap and water after handling. If accidental eye contact occurs, immediately rinse eyes thoroughly with water. If irritation persists, seek medical attention. To obtain a Safety Data Sheet(s), contact Elanco US Inc. at 1-800-428-4441.

Animal Safety Warnings: Behavioral signs such as agitation and decreased feed consumption have been reported in cattle fed ractopamine hydrochloride.

Additional Recommendations: See the Beef Quality Assurance (BQA) recommendations for best practices in cattle care and handling during Optaflexx feeding, transport, and marketing to help mitigate the behavioral signs stated in the Animal Safety Warnings section above.

Storage and Handling: Store at less than or equal to 25°C (77°F). Excursions to 40°C (104°F) are acceptable. Avoid excessive moisture.

Expiration Date and Lot Number are printed on the bag.

Not to be used after the expiry date.

QUESTIONS/COMMENTS? To report side effects, access medical information, or obtain additional product information, contact Elanco US Inc. at 1-800-428-4441.

For additional information about reporting side effects for animal drugs, contact FDA at 1-888-FDA-VETS or www.fda.gov/reportanimalae.

Restricted Drug (California) - Use Only as Directed

Approved by FDA under NADA # 141-221

Optaflexx™ 45

Manufactured for: Elanco US, Inc

Indianapolis, IN 46221

Optaflexx, Elanco and the diagonal bar logo are trademarks of Elanco or its affiliates.

© 2025 Elanco or its affiliates

Revision Date: NOV/2025

BG243489X
YL243489X

Lot
DOM
EXP

Principal Display Panel – 25 lb Bag Label

Elanco™

AF0630

Optaflexx™45

(ractopamine hydrochloride Type A medicated article)

For use in Feeds For Growing Beef Steers and
Heifers Fed in Confinement for Slaughter Only

Net Weight 25 lb
(11.34 kg)